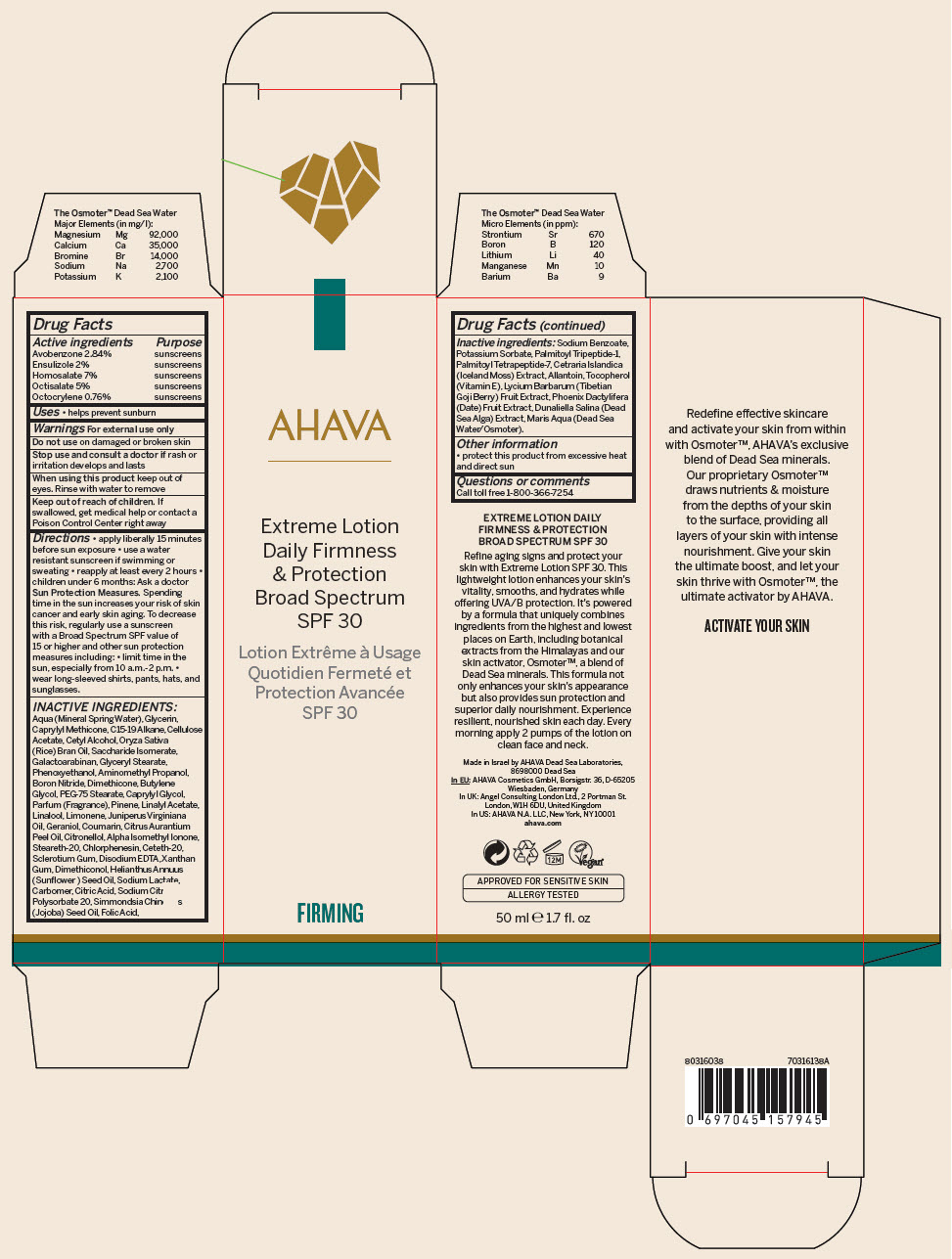 DRUG LABEL: AHAVA Extreme Daily Firmness And Protection Broad Spectrum SPF30
NDC: 60289-305 | Form: LOTION
Manufacturer: AHAVA Dead Sea Laboratories Ltd
Category: otc | Type: HUMAN OTC DRUG LABEL
Date: 20250801

ACTIVE INGREDIENTS: Homosalate 3.5 g/50 mL; Octisalate 2.5 g/50 mL; Avobenzone 1.42 g/50 mL; Ensulizole 1 g/50 mL; Octocrylene 0.38 g/50 mL
INACTIVE INGREDIENTS: Water; Glycerin; C15-19 Alkane; Caprylyl Trisiloxane; Cetyl Alcohol; Rice Bran Oil; Saccharide Isomerate; Cellulose Acetate; CETRARIA ISLANDICA WHOLE; Allantoin; .Alpha.-Tocopherol; Date; Folic Acid; Palmitoyl Tetrapeptide-7; Palmitoyl Tripeptide-1; Galactoarabinan; Sunflower Oil; Glyceryl Monostearate; Phenoxyethanol; Aminomethylpropanol; Boron Nitride; Dimethicone; Butylene Glycol; Ceteth-20; Steareth-20; Caprylyl Glycol; PEG-75 Stearate; Chlorphenesin; Xanthan Gum; Edetate Disodium Anhydrous; HYDROGENATED POLYDECENE TYPE I; Betasizofiran; CARBOMER HOMOPOLYMER, UNSPECIFIED TYPE; Geraniol; .Beta.-Citronellol, (R)-; Coumarin; Limonene, (+)-; Linalool, (+/-)-; Citric Acid Monohydrate; Sodium Citrate, Unspecified Form; Polysorbate 20; Potassium Sorbate; Sodium Benzoate; LYSOPHOSPHATIDYLCHOLINE, SOYBEAN; ISOMETHYL-.ALPHA.-IONONE; LYCIUM BARBARUM FRUIT; DUNALIELLA SALINA; Sodium Lactate

AHAVA Extreme Daily Firmness And Protection Broad Spectrum SPF30

Drug Facts

ACTIVE INGREDIENT

Active ingredients | Purpose
Avobenzone 2.84% | sunscreens
Ensulizole 2% | sunscreens
Homosalate 7% | sunscreens
Octisalate 5% | sunscreens
Octocrylene 0.76% | sunscreens

Uses

- helps prevent sunburn

Warnings

For external use only

Do not use on damaged or broken skin

Stop use and consult a doctor if rash or irritation develops and lasts

When using this product keep out of eyes. Rinse with water to remove

Keep out of reach of children. If swallowed, get medical help or contact a Poison Control Center right away

Directions

- apply liberally 15 minutes before sun exposure
- use a water resistant sunscreen if swimming or sweating
- reapply at least every 2 hours
- children under 6 months: Ask a doctor

Sun Protection Measures. Spending time in the sun increases your risk of skin cancer and early skin aging. To decrease this risk, regularly use a sunscreen with a Broad Spectrum SPF value of 15 or higher and other sun protection measures including:

- limit time in the sun, especially from 10 a.m.-2 p.m.
- wear long-sleeved shirts, pants, hats, and sunglasses.

INACTIVE INGREDIENTS

Aqua (Mineral Spring Water), Glycerin, Caprylyl Methicone, C15-19 Alkane, Cellulose Acetate, Cetyl Alcohol, Oryza Sativa (Rice) Bran Oil, Saccharide Isomerate, Galactoarabinan, Glyceryl Stearate, Phenoxyethanol, Aminomethyl Propanol, Boron Nitride, Dimethicone, Butylene Glycol, PEG-75 Stearate, Caprylyl Glycol, Parfum (Fragrance), Pinene, Linalyl Acetate, Linalool, Limonene, Juniperus Virginiana Oil, Geraniol, Coumarin, Citrus Aurantium Peel Oil, Citronellol, Alpha Isomethyl Ionone, Steareth-20, Chlorphenesin, Ceteth-20, Sclerotium Gum, Disodium EDTA, Xanthan Gum, Dimethiconol, Helianthus Annuus (Sunflower) Seed Oil, Sodium Lactate, Carbomer, Citric Acid, Sodium Citrate, Polysorbate 20, Simmondsia Chinensis (Jojoba) Seed Oil, Folic Acid, Sodium Benzoate, Potassium Sorbate, Palmitoyl Tripeptide-1, Palmitoyl Tetrapeptide-7, Cetraria Islandica (Iceland Moss) Extract, Allantoin, Tocopherol (Vitamin E), Lycium Barbarum (Tibetian Goji Berry) Fruit Extract, Phoenix Dactylifera (Date) Fruit Extract, Dunaliella Salina (Dead Sea Alga) Extract, Maris Aqua (Dead Sea Water/Osmoter).

Other information

- protect this product from excessive heat and direct sun

Questions or comments

Call toll free 1-800-366-7254

PRINCIPAL DISPLAY PANEL - 50 ml Bottle Carton

AHAVA

Extreme Lotion
Daily Firmness
& Protection
Broad Spectrum
SPF 30

FIRMING